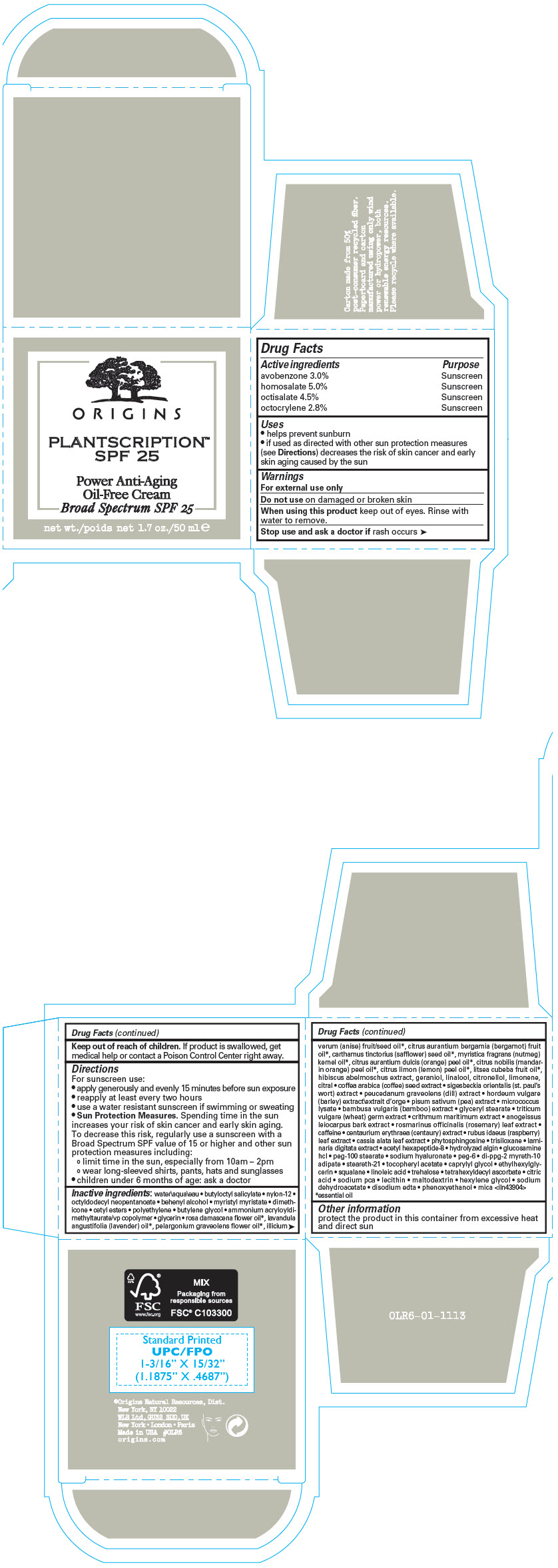 DRUG LABEL: PLANTSCRIPTION SPF 25 POWER ANTI-AGING oil FREE BROAD SPECTRUM
NDC: 59427-012 | Form: CREAM
Manufacturer: ORIGINS NATURAL RESOURCES INC.
Category: otc | Type: HUMAN OTC DRUG LABEL
Date: 20231108

ACTIVE INGREDIENTS: AVOBENZONE 30 mg/1 mL; HOMOSALATE 50 mg/1 mL; OCTISALATE 45 mg/1 mL; OCTOCRYLENE 28 mg/1 mL
INACTIVE INGREDIENTS: WATER; BUTYLOCTYL SALICYLATE; NYLON-12; OCTYLDODECYL NEOPENTANOATE; DOCOSANOL; MYRISTYL MYRISTATE; DIMETHICONE; CETYL ESTERS WAX; HIGH DENSITY POLYETHYLENE; BUTYLENE GLYCOL; AMMONIUM ACRYLOYLDIMETHYLTAURATE/VP COPOLYMER; GLYCERIN; ROSA X DAMASCENA FLOWER OIL; LAVENDER OIL; PELARGONIUM GRAVEOLENS FLOWER OIL; STAR ANISE OIL; BERGAMOT OIL; SAFFLOWER OIL; NUTMEG OIL; ORANGE OIL, COLD PRESSED; MANDARIN OIL; LEMON OIL, COLD PRESSED; LITSEA OIL; GERANIOL; LINALOOL, (+/-)-; .BETA.-CITRONELLOL, (R)-; LIMONENE, (+)-; CITRAL; ARABICA COFFEE BEAN; HORDEUM VULGARE WHOLE; PEA; BAMBUSA VULGARIS TOP; GLYCERYL MONOSTEARATE; WHEAT GERM; CRITHMUM MARITIMUM WHOLE; ANOGEISSUS LEIOCARPUS BARK; ROSEMARY; CAFFEINE; CENTAURIUM ERYTHRAEA; RUBUS IDAEUS LEAF; SENNA ALATA LEAF; PHYTOSPHINGOSINE; TRISILOXANE; LAMINARIA DIGITATA; ACETYL HEXAPEPTIDE-8; GLUCOSAMINE HYDROCHLORIDE; PEG-100 STEARATE; HYALURONATE SODIUM; POLYETHYLENE GLYCOL 300; DI-PPG-2 MYRETH-10 ADIPATE; STEARETH-21; .ALPHA.-TOCOPHEROL ACETATE; CAPRYLYL GLYCOL; ETHYLHEXYLGLYCERIN; SQUALANE; LINOLEIC ACID; TREHALOSE; TETRAHEXYLDECYL ASCORBATE; CITRIC ACID MONOHYDRATE; SODIUM PYRROLIDONE CARBOXYLATE; MALTODEXTRIN; HEXYLENE GLYCOL; SODIUM DEHYDROACETATE; EDETATE DISODIUM ANHYDROUS; PHENOXYETHANOL; MICA; LECITHIN, SOYBEAN; PEG-6 DISTEARATE; LAMINARIA DIGITATA HYDROLYZED ALGINIC ACID; CATALASE (MICROCOCCUS LUTEUS); DILL; SIGESBECKIA ORIENTALIS FLOWERING TOP

PLANTSCRIPTION™ SPF 25 POWER ANTI-AGING OIL FREE BROAD SPECTRUM CREAM

Drug Facts

ACTIVE INGREDIENT

Active ingredients | Purpose
avobenzone 3.0% | Sunscreen
homosalate 5.0% | Sunscreen
octisalate 4.5% | Sunscreen
octocrylene 2.8% | Sunscreen

Uses

- helps prevent sunburn
- if used as directed with other sun protection measures (see Directions) decreases the risk of skin cancer and early skin aging caused by the sun

Warnings

For external use only

Do not use on damaged or broken skin

When using this product keep out of eyes. Rinse with water to remove.

Stop use and ask a doctor if rash occurs

Keep out of reach of children. If product is swallowed, get medical help or contact a Poison Control Center right away.

Directions

For sunscreen use:

- apply generously and evenly 15 minutes before sun exposure
- reapply at least every two hours
- use a water resistant sunscreen if swimming or sweating
- Sun Protection Measures. Spending time in the sun increases your risk of skin cancer and early skin aging. To decrease this risk, regularly use a sunscreen with a Broad Spectrum SPF value of 15 or higher and other sun protection measures including:
  - limit time in the sun, especially from 10am – 2pm
  - wear long-sleeved shirts, pants, hats and sunglasses
- children under 6 months of age: ask a doctor

Inactive ingredients

water\aqua\eau • butyloctyl salicylate • nylon-12 • octyldodecyl neopentanoate • behenyl alcohol • myristyl myristate • dimethicone • cetyl esters • polyethylene • butylene glycol • ammonium acryloyldimethyltaurate/vp copolymer • glycerin • rosa damascena flower oil [essential oil] , lavandula angustifolia (lavender) oil , pelargonium graveolens flower oil , illicium verum (anise) fruit/seed oil , citrus aurantium bergamia (bergamot) fruit oil , carthamus tinctorius (safflower) seed oil , myristica fragrans (nutmeg) kernel oil , citrus aurantium dulcis (orange) peel oil , citrus nobilis (mandarin orange) peel oil , citrus limon (lemon) peel oil , litsea cubeba fruit oil , hibiscus abelmoschus extract, geraniol, linalool, citronellol, limonene, citral • coffea arabica (coffee) seed extract • sigesbeckia orientalis (st. paul's wort) extract • peucedanum graveolens (dill) extract • hordeum vulgare (barley) extract\extrait d'orge • pisum sativum (pea) extract • micrococcus lysate • bambusa vulgaris (bamboo) extract • glyceryl stearate • triticum vulgare (wheat) germ extract • crithmum maritimum extract • anogeissus leiocarpus bark extract • rosmarinus officinalis (rosemary) leaf extract • caffeine • centaurium erythraea (centaury) extract • rubus idaeus (raspberry) leaf extract • cassia alata leaf extract • phytosphingosine • trisiloxane • laminaria digitata extract • acetyl hexapeptide-8 • hydrolyzed algin • glucosamine hcl • peg-100 stearate • sodium hyaluronate • peg-6 • di-ppg-2 myreth-10 adipate • steareth-21 • tocopheryl acetate • caprylyl glycol • ethylhexylglycerin • squalane • linoleic acid • trehalose • tetrahexyldecyl ascorbate • citric acid • sodium pca • lecithin • maltodextrin • hexylene glycol • sodium dehydroacetate • disodium edta • phenoxyethanol • mica <iln43904>

Other information

protect the product in this container from excessive heat and direct sun

PRINCIPAL DISPLAY PANEL - 50 ml Jar Carton

ORIGINS

PLANTSCRIPTION™
SPF 25

Power Anti-Aging
Oil-Free Cream

Broad Spectrum SPF 25

net wt. 1.7 oz./50 ml e